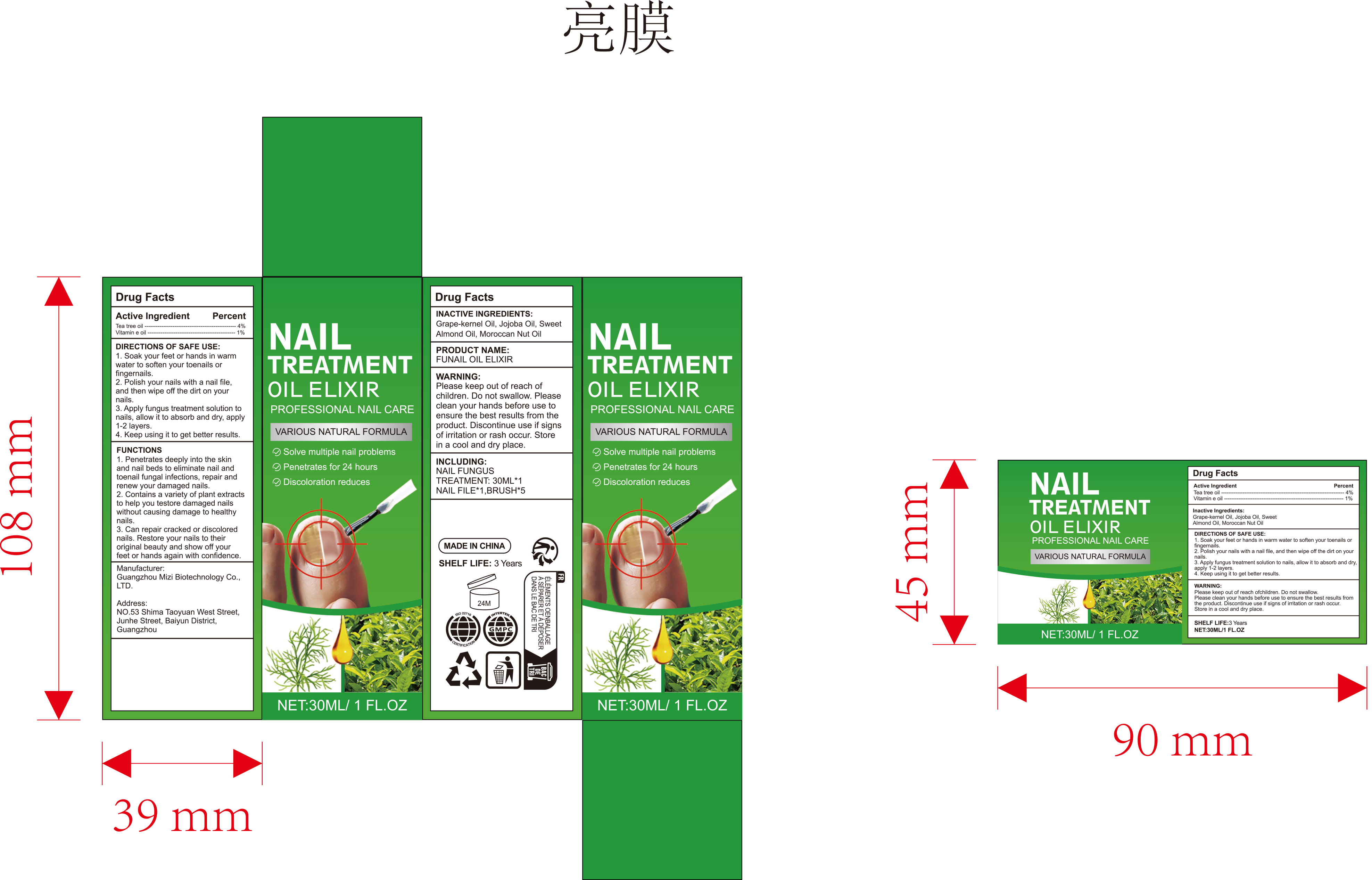 DRUG LABEL: NAIL TREATMENT Oil Elixirs
NDC: 84896-003 | Form: LIQUID
Manufacturer: Guangzhou Mizi Biotechnology Co., LTD.
Category: otc | Type: HUMAN OTC DRUG LABEL
Date: 20251217

ACTIVE INGREDIENTS: TEA TREE OIL 0.04 g/1 mL; .ALPHA.-TOCOPHEROL 0.01 g/1 mL
INACTIVE INGREDIENTS: GRAPE SEED OIL; JOJOBA OIL; ALMOND OIL; ARGAN OIL

84896-003 NAIL TREATMENT OIL ELIXIR

ACTIVE INGREDIENT

Tea tree oil 4%
Vitamin e oil 1%

PURPOSE

Nail care

INDICATIONS AND USAGE

1. Penetrates deeply into the skinand nail beds to eliminate nail andtoenail fungal infections, repair andrenew your damaged nails.
2. Contains a variety of plant extractsto help you testore damaged nailswithout causing damage to healthynails.
3. Can repair cracked or discolorednails. Restore your nails to theiroriginal beauty and show off yourfeet or hands again with confidence.

WARNINGS

For external use only

DO NOT USE

Do not swallow. Please clean your hands before use to ensure the best results from the product.

WHEN USING

Please clean your hands before use to ensure the best results from the product.

STOP USE

Discontinue use if signs of irritation or rash occur.

Please keep out of reach of children.

DOSAGE AND ADMINISTRATION

1. Soak your feet or hands in warm water to soften your toenails or fingernails.
2. Polish your nails with a nail file.and then wipe off the dirt on your nails.
3.Apply fungus treatment solution to nails, allow it to absorb and dry, apply 1-2 layers.
4. Keep using it to get better results

INACTIVE INGREDIENT

Grape-kernel Oil, Jojoba Oil, Sweet Almond Oil, Moroccan Nut Oil